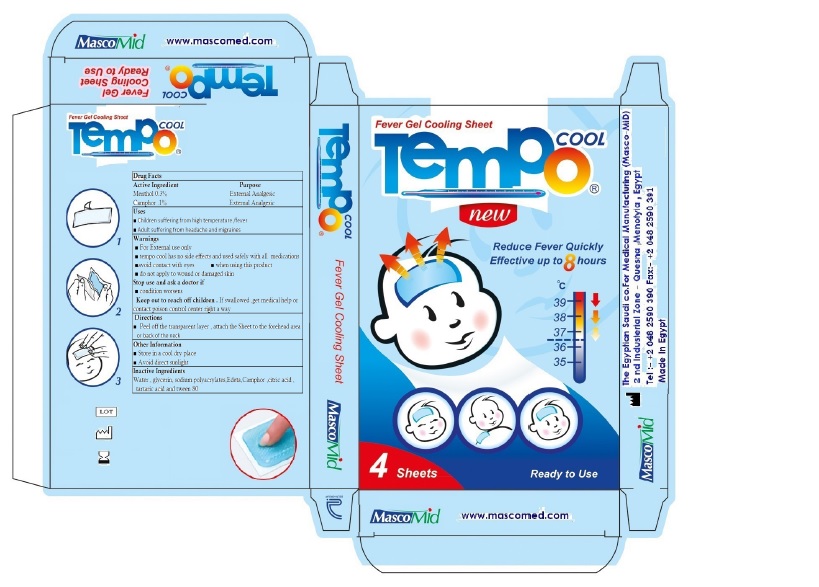 DRUG LABEL: Tempo cool
NDC: 72602-003 | Form: PATCH
Manufacturer: The Egyptian Saudi Co. For Medical Manufacturing (Masco-Mid) S.A.E
Category: otc | Type: HUMAN OTC DRUG LABEL
Date: 20251006

ACTIVE INGREDIENTS: MENTHOL 3 mg/1 g; CAMPHOR (NATURAL) 1 mg/1 g
INACTIVE INGREDIENTS: GLYCERIN; SODIUM POLYACRYLATE (2500000 MW); CITRIC ACID MONOHYDRATE; TARTARIC ACID; POLYSORBATE 80; CARBOXYMETHYLCELLULOSE SODIUM (0.9 CARBOXYMETHYL SUBSTITUTION PER SACCHARIDE; 600 MPA.S AT 2%); EDETATE DISODIUM; POLYACRYLIC ACID (800000 MW); WATER

TempoCOOL

Purpose Section

- Children suffering from high temperature or fever
- Adults suffering from headache and migrain

Warnings

- FOR EXTERNAL USE ONLY
- Tempo cool has no side effects and used safely with all medications.
- Avoid contacts with eyes.
- Do not bandage tightly.
- Do not apply to wound or damaged skin

Dosage

- One sheet for 8 hours.

Directions

- Peel off the transparent layer,attach Sheet to the forehead area or back of the neck.

Stop use and ask doctor

- If condition worsens

Storage

- Store in a cool dry place.
- Avoid direct sunlight.

KEEP OUT OF REACH OF CHILDREN

If swallowed, get medical help or contact a Poison Control Center right a way

Active Ingredient section

Menthol 0.3 %

Camphor. 1%

Inactive Ingredient section

Glycerin ,Sodium polyacrylate , Anhydrous citric acid ,Tartaric acid ,Poly sorbate -80 (tween 80) ,
EDETA ,Water.